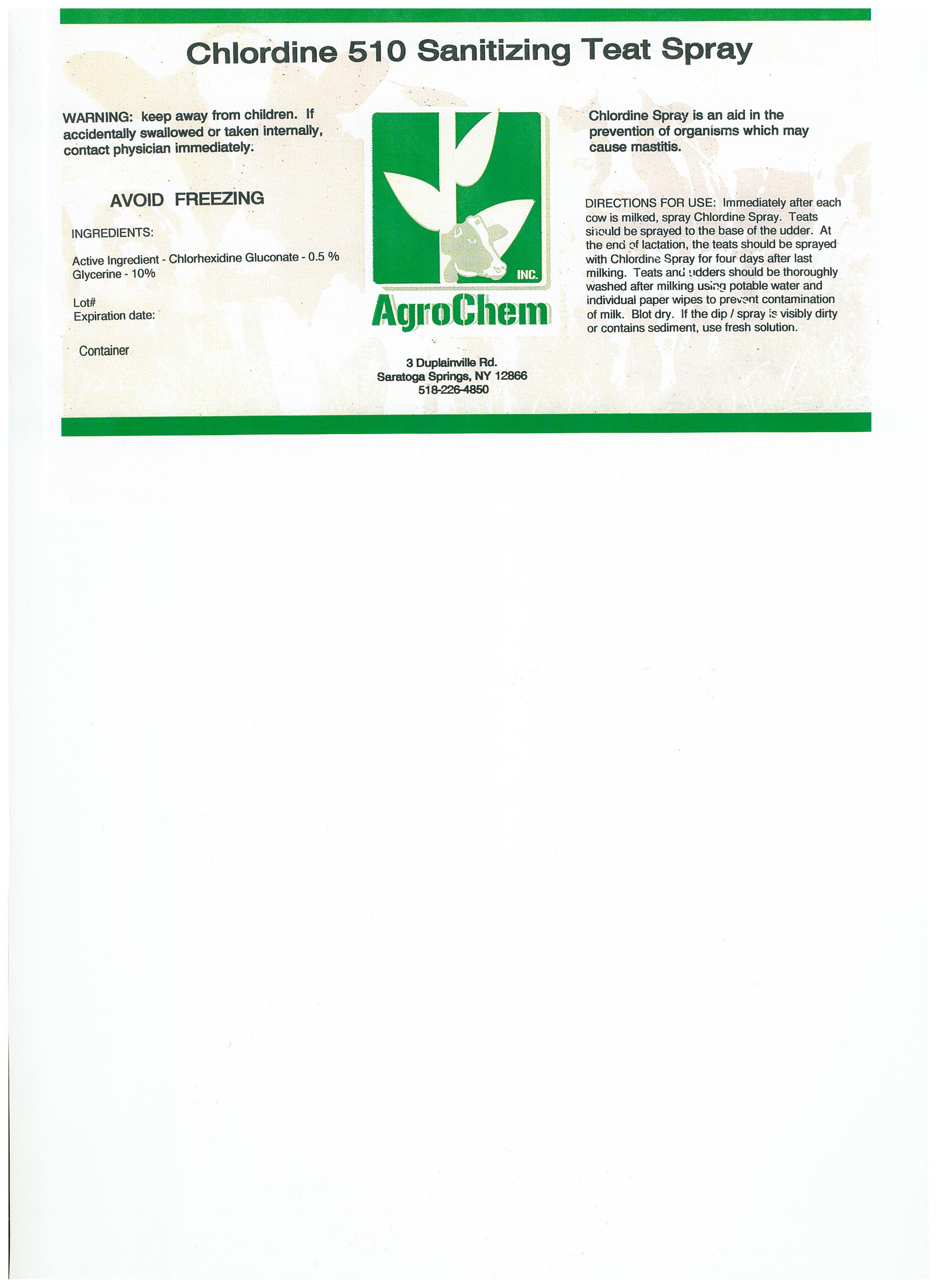 DRUG LABEL: Chlordine 510
NDC: 17307-5100 | Form: SPRAY
Manufacturer: AgroChem Inc
Category: animal | Type: OTC ANIMAL DRUG LABEL
Date: 20130729

ACTIVE INGREDIENTS: CHLORHEXIDINE GLUCONATE .0275 kg/1 kg
INACTIVE INGREDIENTS: WATER .86 kg/1 kg; GLYCERIN .10 kg/1 kg; NONOXYNOL-12 .01 kg/1 kg

Chlordine 510

WARNINGS

WARNING: Keep away from children. If

accidentally swallowed or taken internally

contact physician immediately.

AVOID FREEZING

ACTIVE INGREDIENT

INGREDIENTS:

Active Ingredient - Chlorhexidine Gluconate 0.5%

Glycerine 10%

DESCRIPTION

Chlordine Spray is an aid in the

prevention of organisms which may

cause mastitis

DIRECTIONS FOR USE: Immediately after each

cow is milked, spray Chlordine Spray. Teats

should be sprayed to the base of the udder. At

the end of lactation, the teats should be sprayed

with Chlordine Spray for four days after last

milking. Teats and udders should be thoroughly

washed after milking using potable water and

individual paper wipes to prevent contamination

of milk. Blot dry. If the dip/spray is visibly dirty

or contains sediment. use fresh solution.